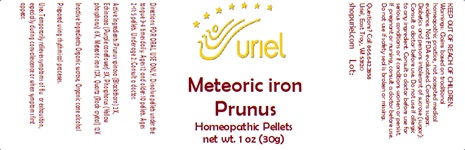 DRUG LABEL: Meteoric Iron Prunus
NDC: 48951-7188 | Form: PELLET
Manufacturer: Uriel Pharmacy Inc
Category: homeopathic | Type: HUMAN OTC DRUG LABEL
Date: 20241203

ACTIVE INGREDIENTS: PRUNUS SPINOSA FLOWER BUD 2 [hp_X]/1 1; ECHINACEA PALLIDA 3 [hp_X]/1 1; PHOSPHORUS 6 [hp_X]/1 1; SILICON DIOXIDE 12 [hp_X]/1 1; IRON 12 [hp_X]/1 1
INACTIVE INGREDIENTS: SUCROSE; ALCOHOL

Meteoric Iron Prunus

INDICATIONS AND USAGE

Directions: FOR ORAL USE ONLY.

DOSAGE AND ADMINISTRATION

Dissolve pellets under the tongue 3-4 times daily. Ages 12 and older: 10 pellets. Ages 2-11: 5 pellets. Under age 2: Consult a doctor.

ACTIVE INGREDIENT

Active Ingredients: Prunus spinosa (Blackthorn) 2X, Echinacea (Purple coneflower) 3X, Phosphorus (Yellow phosphorus) 6X, Meteoric iron 12X, Quartz (Rock crystal) 12X

Inactive Ingredient: Sucrose, Organic cane alcohol

Prepared using rhythmical processes.

PURPOSE

Uses: Temporarily relieves symptoms of flu or exhaustion, especially during convalescence or when symptoms first appear.

KEEP OUT OF REACH OF CHILDREN.

WARNINGS

Warnings: Claims based on traditional homeopathic practice, not accepted medical evidence. Not FDA evaluated. Contains sugar. Diabetics and persons intolerant of sucrose (sugar): Consult a doctor before use. Do not use if allergic to any ingredient. Consult a doctor before use for serious conditions or if conditions worsen or persist. If pregnant or nursing, consult a doctor before use. Do not use if safety seal is broken or missing.

Questions? Call 866.642.2858
Uriel, East Troy, WI 53120
shopuriel.com Lot: